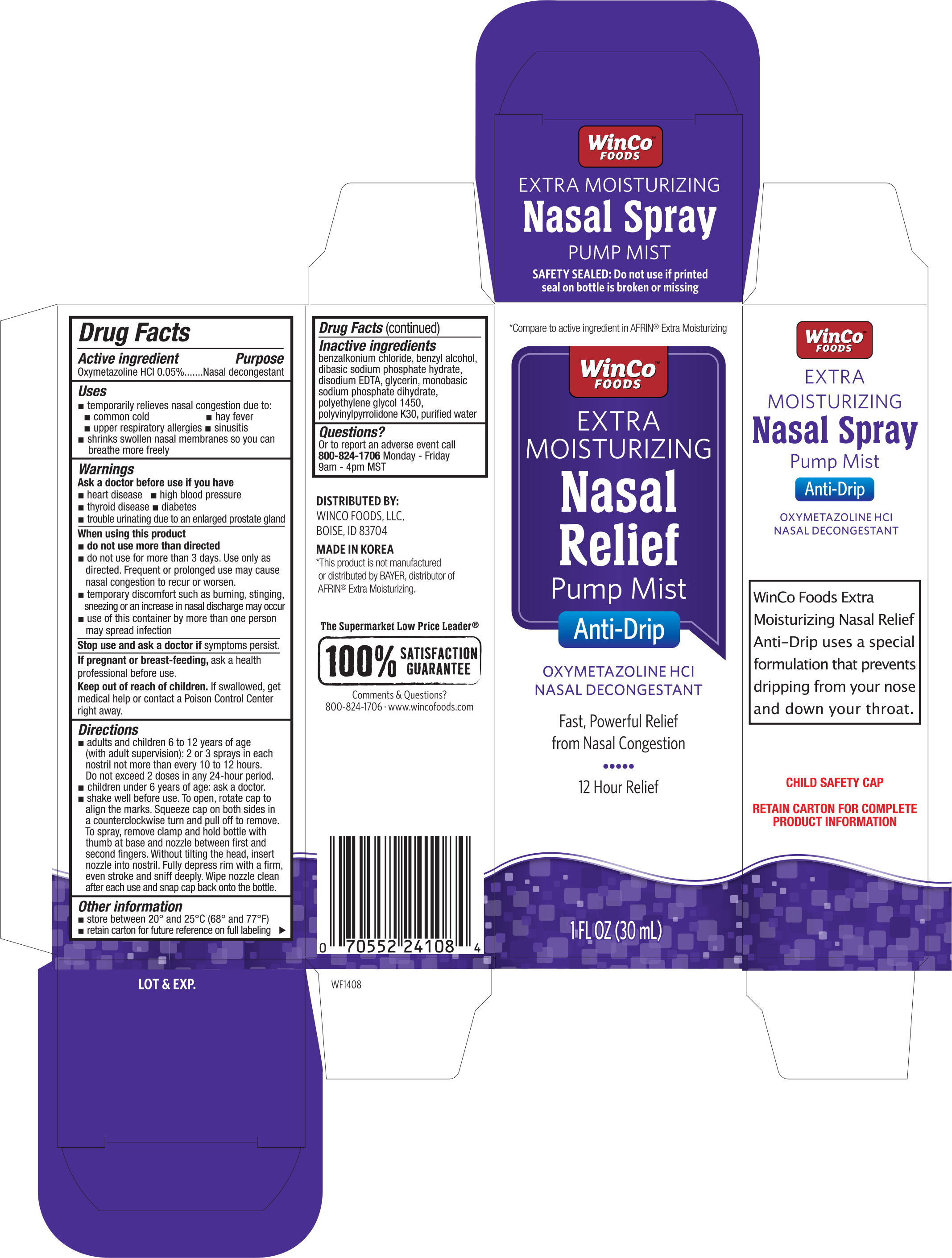 DRUG LABEL: WinCo Foods Extra Moisturizing Nasal Relief
NDC: 67091-191 | Form: SPRAY
Manufacturer: WinCo Foods, LLC
Category: otc | Type: HUMAN OTC DRUG LABEL
Date: 20161102

ACTIVE INGREDIENTS: OXYMETAZOLINE HYDROCHLORIDE .005 g/100 mL
INACTIVE INGREDIENTS: BENZALKONIUM CHLORIDE; BENZYL ALCOHOL; SODIUM PHOSPHATE, DIBASIC; EDETATE DISODIUM; GLYCERIN; SODIUM PHOSPHATE, MONOBASIC, DIHYDRATE; POLYETHYLENE GLYCOL 1450; POVIDONE K30; WATER

Active Ingredient Purpose

Oxymetazoline HCI 0.05%----------------------------------------------------------------------- Nasal decongestant

Uses

- temporarily relieves nasal congestion due to:
- common cold
- hay fever
- upper respiratory allergies
- sinusitis
- shrinks swollen nasal membranes so you can breathe more freely

Warnings

Ask a doctor before use if you have

- heart disease
- high blood pressure
- thyroid disease
- diabetes
- trouble urinating due to an enlarged prostate gland

When using this product

- do not use more than directed
- do not use more than 3 days. Frequent or prolonged use may cause nasal congestion to recur or worsen
- temporary discomfort such as burning, stinging, sneezing or an increase in nasal discharge may occur
- use of this container by more than one person may spread infection

Stop use and ask a doctor if symptoms persist

PREGNANCY OR BREAST FEEDING

If pregnant or breast-feeding, ask a health professional before use.

Keep out of reach of children. If swallowed, get medical help or contact a Poison Control Center right away.

INDICATIONS AND USAGE

Direction

- adults and children 6 to 12 years of age (with adult supervision): 2 or 3 sprays in each nostril not more than every 10 to 12 hours. Do not exceed 2 doses in any 24-hour period.
- Children under 6 years of age: ask a doctor
- Shake well before use. To open, rotate cap to align the marks. Squeeze cap on both sides in a counterclockwise turn and pull off to remove. To spray, remove clamp and hold bottle with thumb at base and nozzle between first and second fingers. Without tilting the head, insert nozzle into nostril. Fully depress rim with a firm, even stroke and sniff deeply. Wipe nozzle clean after each use and snap cap back onto the bottle.

Other information

- Store between 20° and 25°C (68° and 77°F)
- Retain carton for future reference on fully labeling

Inactive ingredients

benzalkonium chloride, benzyl alcohol, dibasic sodium phosphate hydrate, disodium EDTA, glycerin, monobasic sodium phosphate dihydrate, polyethylene glycol 1450, polyvinylpyrrolidone K30, purified water

DOSAGE AND ADMINISTRATION

DISTRIBUTED BY:

WINCO FODDS, LLC,

BOISE, ID 83704

MADE IN KOREA